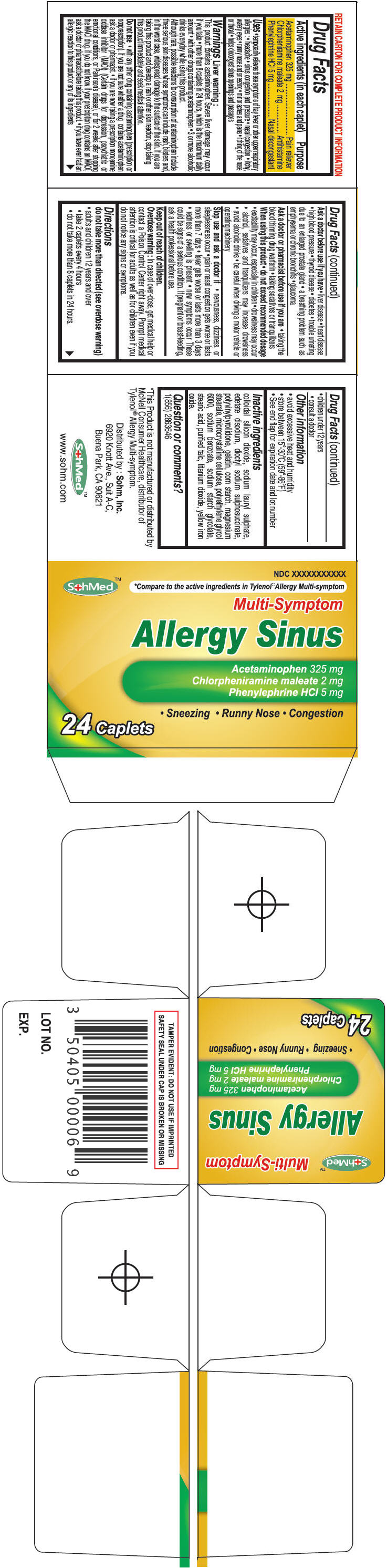 DRUG LABEL: SohMed Allergy Sinus
NDC: 50405-003 | Form: TABLET
Manufacturer: SOHM Inc.
Category: otc | Type: HUMAN OTC DRUG LABEL
Date: 20130819

ACTIVE INGREDIENTS: Acetaminophen 325 mg/1 1; Chlorpheniramine maleate 2 mg/1 1; Phenylephrine Hydrochloride 5 mg/1 1
INACTIVE INGREDIENTS: SILICON DIOXIDE; SODIUM LAURYL SULFATE; EDETATE DISODIUM; DOCUSATE SODIUM; POVIDONE K90; GELATIN; STARCH, CORN; MAGNESIUM STEARATE; CELLULOSE, MICROCRYSTALLINE; POLYETHYLENE GLYCOL 6000; SODIUM BENZOATE; SODIUM STARCH GLYCOLATE TYPE A CORN; STEARIC ACID; TALC; TITANIUM DIOXIDE; FERRIC OXIDE YELLOW

SohMed™ Allergy Sinus

Drug Facts

ACTIVE INGREDIENT

Active ingredients (in each caplet) | Purpose
Acetaminophen 325 mg | Pain reliever
Chlorpheniramine maleate 2 mg | Antihistamine
Phenylephrine HCl 5 mg | Nasal decongestant

Uses

- temporarily relieves these symptoms of hay fever or other upper respiratory allergies :
  - headache
  - sinus congestion and pressure
  - nasal congestion
  - itchy, watery eyes
  - runny nose and sneezing
  - minor aches and pains
  - itching of the nose or throat
  - helps decongest sinus openings and passages

Warnings

Liver warning

This product contains acetaminophen. Severe liver damage may occur if you take

- more than 8 caplets in 24 hours, which is the maximum daily amount
- with other drugs containing acetaminophen
- 3 or more alcoholic drinks everyday while using this product.

Although rare, possible reactions to consumption of acetaminophen include three serious skin diseases whose symptoms can include rash, blisters and, in the worst case, widespread damage to the surface of the skin. If you are taking this product and develop a rash or other skin reaction, stop taking this product immediately and seek medical attention.

Do not use

- with any other drug containing acetaminophen (prescription or nonprescription). If you are not sure whether a drug contains acetaminophen ask a doctor or pharmacist.
- if you are now taking a prescription monoamine oxidase inhibitor (MAOI) (Certain drugs for depression, pscychiatric or emotional conditions, or Parkinson's disease), or for 2 weeks after stopping the MAOI drug. if you do not know if your prescription drug contains an MAOI, ask a doctor or pharmacist before taking this product.
- if you have ever had an allergic reaction to this product or any of its ingredients

Ask a doctor before use if you have

- liver disease
- heart disease
- high blood pressure
- thyroid disease
- diabetes
- trouble urinating due to an enlarged prostate gland
- a breathing problem such as emphysema or chronic bronchitis
- glaucoma

Ask a doctor or pharmacist before use if you are

- taking the blood thinning drug warfarin
- taking sedatives or tranquilizers

When using this product

- do not exceed recommended dosage
- excitability may occur, especially in children
- drowsiness may occur
- alcohol, sedatives and tranquilizers may increase drowsiness
- avoid alcoholic drinks
- be careful when driving a motor vehicle or operating machinery

Stop use and ask a doctor if

- nervousness, dizziness, or sleeplessness occur
- pain or nasal congestion gets worse or lasts more than 7 days
- fever gets worse or lasts more than 3 days
- redness or swelling is present
- new symptoms occur

These could be signs of a serious condition.

PREGNANCY OR BREAST FEEDING

If pregnant or breast-feeding, ask a health professional before use.

Keep out of reach of children.

Overdose warning

In case of over-dose, get medical help or contact a Poison Control Center right away. Prompt medical attention is critical for adults as well as for children even if you do not notice any signs or symptoms.

Directions

do not take more than directed (see overdose warning)

- adults and children 12 years and over
  - take 2 caplets every 4 hours
  - do not take more than 8 caplets in 24 hours.
- children under 12 years
  - consult a doctor

Other information

- avoid excessive heat and humidity
- store between 15°-30°C (59°-86°F)
- See end flap for expiration date and lot number

Inactive ingredients

colloidal silicon dioxide, sodium lauryl sulphate, edetate disodium, dioctyl sodium sulphosuccinate, polyvinylpyrollidone, gelatin, corn starch, magnesium stearate, microcrystalline cellulose, polyethylene glycol 6000, sodium benzoate, sodium starch glycolate, stearic acid, purified talc, titanium dioxide, yellow iron oxide.

Question or comments?

1(856) 2863646

Distributed by : Sohm, Inc.
6920 Knott Ave., Suit A-C,
Buena Park, CA 90621

PRINCIPAL DISPLAY PANEL - 24 Caplet Bottle Carton

NDC XXXXXXXXXXX

SohMed™
*Compare to the active ingredients in Tylenol:: Allergy Multi-symptom

Multi-Symptom

Allergy Sinus

Acetaminophen 325 mg
Chlorpheniramine maleate 2 mg
Phenylephrine HCl 5 mg

• Sneezing • Runny Nose • Congestion

24 Caplets